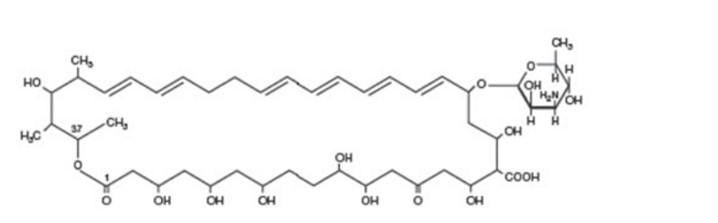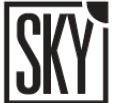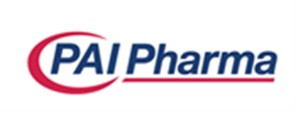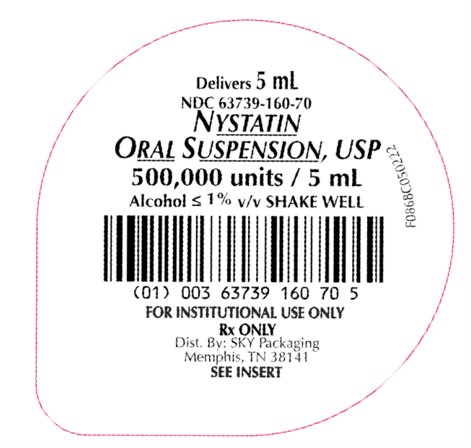 DRUG LABEL: Nystatin
NDC: 63739-160 | Form: SUSPENSION
Manufacturer: McKesson Corporation dba SKY Packaging
Category: prescription | Type: HUMAN PRESCRIPTION DRUG LABEL
Date: 20260227

ACTIVE INGREDIENTS: NYSTATIN 100000 [USP'U]/1 mL
INACTIVE INGREDIENTS: ALCOHOL; ANHYDROUS CITRIC ACID; D&C YELLOW NO. 10; FD&C RED NO. 40; GLYCERIN; METHYLPARABEN; POTASSIUM PHOSPHATE, DIBASIC; PROPYLENE GLYCOL; PROPYLPARABEN; WATER; SUCROSE; MAGNESIUM ALUMINUM SILICATE

Nystatin Oral Suspension USP
[100,000 units per mL]

Rx Only

DESCRIPTION

Nystatin is an antimycotic polyene antibiotic obtained from Streptomyces noursei.

Structural Formula:

Nystatin Oral Suspension USP, for oral administration, contains 100,000 USP Nystatin Units per mL. Inactive ingredients: alcohol (≤ 1% v/v), artificial peppermint flavor, cherry flavor, citric acid, D&C Yellow No. 10, FD&C Red No. 40, glycerin, magnesium aluminum silicate, methylparaben, potassium phosphate dibasic, propylene glycol, propylparaben, purified water and sucrose.

CLINICAL PHARMACOLOGY

Pharmacokinetics

Gastrointestinal absorption of nystatin is insignificant. Most orally administered nystatin is passed unchanged in the stool. In patients with renal insufficiency receiving oral therapy with conventional dosage forms, significant plasma concentrations of nystatin may occasionally occur.

Microbiology

Nystatin is both fungistatic and fungicidal in vitro against a wide variety of yeasts and yeast-like fungi. Candida albicans demonstrates no significant resistance to nystatin in vitro on repeated subculture in increasing levels of nystatin; other Candida species become quite resistant. Generally, resistance does not develop in vivo. Nystatin acts by binding to sterols in the cell membrane of susceptible Candida species with a resultant change in membrane permeability allowing leakage of intracellular components. Nystatin exhibits no appreciable activity against bacteria, protozoa, or viruses.

INDICATIONS AND USAGE

Nystatin Oral Suspension is indicated for the treatment of candidiasis in the oral cavity.

CONTRAINDICATIONS

The preparation is contraindicated in patients with a history of hypersensitivity to any of its components.

PRECAUTIONS

General

This medication is not to be used for the treatment of systemic mycoses. Discontinue treatment if sensitization or irritation is reported during use.

Carcinogenesis, Mutagenesis, Impairment of Fertility

No long-term animal studies have been performed to evaluate carcinogenic potential. There also have been no studies to determine mutagenicity or whether this medication affects fertility in males or females.

Pregnancy

Teratogenic Effects

Animal reproduction studies have not been conducted with nystatin oral suspension. It is also not known whether nystatin oral suspension can cause fetal harm when administered to a pregnant woman or can affect reproduction capacity. Nystatin oral suspension should be given to a pregnant woman only if clearly needed.

Nursing Mothers

It is not known whether nystatin is excreted in human milk. Because many drugs are excreted in human milk, caution should be exercised when nystatin is administered to a nursing woman.

Pediatric Use

See DOSAGE AND ADMINISTRATION.

ADVERSE REACTIONS

Nystatin is well tolerated even with prolonged therapy. Oral irritation and sensitization have been reported. (See PRECAUTIONS: General).

Gastrointestinal: Diarrhea (including one case of bloody diarrhea), nausea, vomiting, gastrointestinal upset/disturbances.

Dermatologic: Rash, including urticaria has been reported rarely. Stevens-Johnson syndrome has been reported very rarely.

Other: Tachycardia, bronchospasm, facial swelling, and non-specific myalgia have also been rarely reported.

To report SUSPECTED ADVERSE REACTIONS, contact Pharmaceutical Associates, Inc. at 1-800-845-8210 or FDA at 1-800-FDA-1088 or www.fda.gov/medwatch.

OVERDOSAGE

Oral doses of nystatin in excess of five million units daily have caused nausea and gastrointestinal upset. There have been no reports of serious toxic effects of superinfections (See CLINICAL PHARMACOLOGY, Pharmacokinetics).

DOSAGE AND ADMINISTRATION

INFANTS: 2 mL (200,000 units) four times daily (in infants and young children, use dropper to place one-half of dose in each side of mouth and avoid feeding for 5 to 10 minutes).

NOTE: Limited clinical studies in premature and low birth weight infants indicate that 1 mL four times daily is effective.

CHILDREN AND ADULTS: 4 to 6 mL (400,000 to 600,000 units) four times daily (one-half of dose in each side of mouth). The preparation should be retained in the mouth as long as possible before swallowing.

Continue treatment for at least 48 hours after perioral symptoms have disappeared and cultures demonstrate eradication of Candida albicans.

HOW SUPPLIED

Nystatin Oral Suspension USP, 100,000 USP Nystatin Units per mL, is available in a cherry, peppermint flavored, light creamy yellow, ready-to-use suspension, supplied in the following oral dosage forms:

NDC 63739-160-70: 5mL unit dose cup.
NDC 63739-160-56: Case of 50, 5 mL Unit Dose Cups.
NDC 63739-160-10: Case of 100, 5 mL Unit Dose Cups

Storage

Store at 20° to 25°C (68° to 77°F) [See USP Controlled Room Temperature]. Avoid freezing.

Distributed By:

McKesson Corporation
dba SKY Packaging
Memphis, TN 38141

Manufactured By:

Pharmaceutical
Associates, Inc
www.paipharma.com

I0868C0923 Iss09/2023

PRINCIPAL DISPLAY PANEL - 5 mL Unit Dose Cup Label

Delivers 5 mL

NDC 63739-160-70

NYSTATIN ORAL SUSPENSION, USP

500,000 units/5 mL

Alcohol ≤ 1% v/v SHAKE WELL

Package Not Child-Resistant

Rx ONLY

SEE INSERT